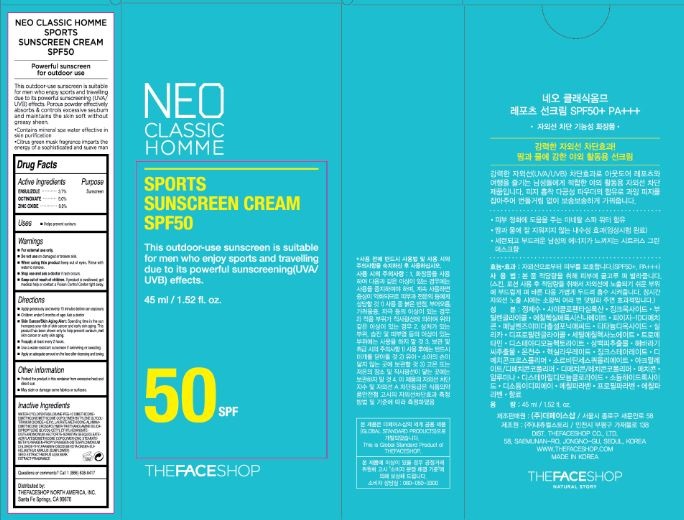 DRUG LABEL: NEO CLASSIC HOMME SPORTS
NDC: 51523-123 | Form: CREAM
Manufacturer: THEFACESHOP CO., LTD.
Category: otc | Type: HUMAN OTC DRUG LABEL
Date: 20141120

ACTIVE INGREDIENTS: ENSULIZOLE 1.7 g/45 mL; OCTINOXATE 2.3 g/45 mL; ZINC OXIDE 4.1 g/45 mL
INACTIVE INGREDIENTS: WATER

NEO CLASSIC HOMME SPORTS 31700111

Active Ingredients

Ensulizole 3.7 %

Octinoxate 5.0 %

Zinc Oxide 9.0 %

Purpose

Sunscreen

Sunscreen

Sunscreen

Warnings

For external use only.

Do not use on damaged or broken skin

When using this product keep out of eyes. Rinse with water to remove.

Stop use and ask a doctor if rash occurs.

Keep out of reach of children.

If product is swallowed, get medical help or contact a Poison Control Center right away.

Directions

Apply generously and evenly 15 minutes before sun exposure.
Children under 6 months of age: Ask a doctor
Apply an adequate amount on the face after cleansing and toning.
Reapply at least every 2 hours.
Skin Cancer/Skin Aging Alert: Spending time in the sun
increases your risk of skin cancer and early skin aging. This
product has been shown only to help prevent sunburn, not
skin cancer or early skin aging.
Use a water-resistant sunscreen if swimming or sweating

Apply an adequate amount on the face after cleansing and toning

OTHER SAFETY INFORMATION

Protect the product in this container from excessive heat and
direct sun.
May stain or damage some fabrics or surfaces.

Inactive Ingredients

WATER•CYCLOPENTASILOXANE•PEG-10 DIMETHICONE•
DIMETHICONE/METHICONE COPOLYMER•BUTYLENE GLYCOL•
TITANIUM DIOXIDE•HEXYL LAURATE•METHICONE•ALUMINA•
DIMETHICONE CROSSPOLYMER•TRIETHANOLAMINE•SILICA•
DIPROPYLENE GLYCOL•CETYL ETHYLHEXANOATE•
DISTEARDIMONIUM HECTORITE•SORBITAN SESQUIOLEATE•
ACRYLATES/DIMETHICONE COPOLYMER•ZINC STEARATE•
METHYLPARABEN•PROPYLPARABEN•DISTEARYLDIMONIUM
CHLORIDE•THYLPARABEN•DISODIUM EDTA•ONSEN-SUI•
HELIANTHUS ANNUUS (SUNFLOWER)
SEED EXTRACT•MORUS ALBA BARK
EXTRACT•FRAGRANCE

Questions or comments? Call 1 (866) 638-8417

Distributed by:

THEFACESHOP NORTH AMERICA, INC.
Santa Fe Springs, CA 90670

PACKAGE LABEL

SPORTS SUNSCREEN CREAM SPF50

This outdoor-use sunscreen is suitable
for men who enjoy sports and travelling
due to its powerful sunscreening(UVA/
UVB) effects.